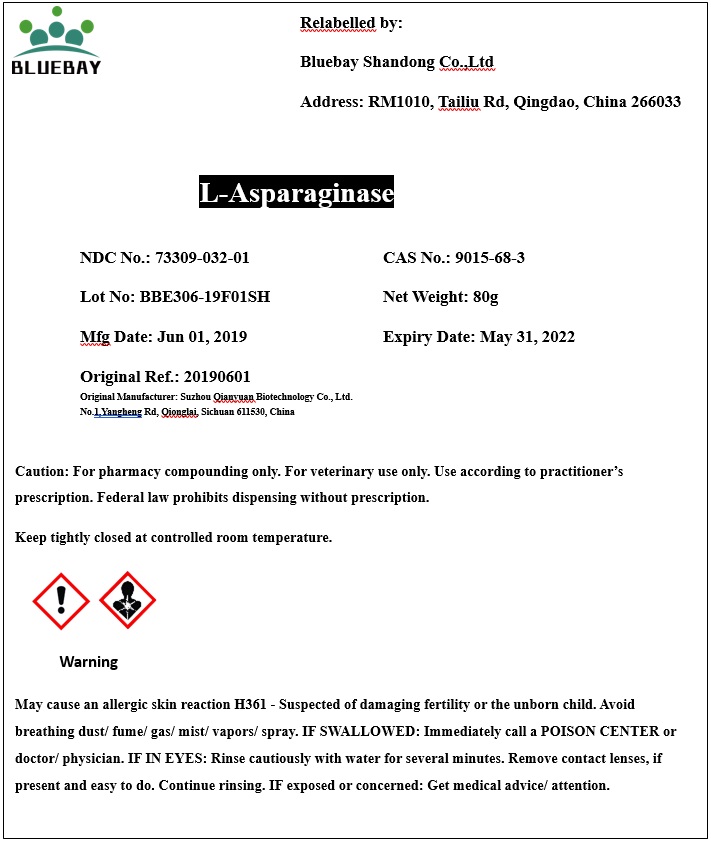 DRUG LABEL: L-Asparaginase
NDC: 73309-032 | Form: POWDER
Manufacturer: BLUEBAY SHANDONG CO.,LTD
Category: other | Type: BULK INGREDIENT
Date: 20190912

ACTIVE INGREDIENTS: ASPARAGINASE 1 g/1 g

L-Asparaginase